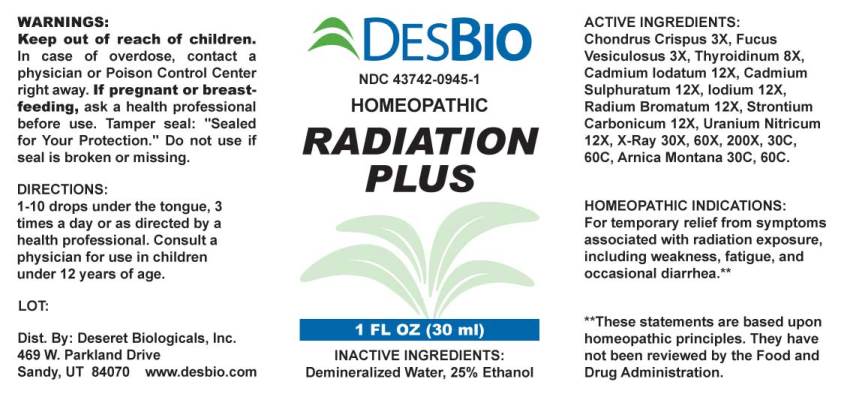 DRUG LABEL: Radiation Plus
NDC: 43742-0945 | Form: LIQUID
Manufacturer: Deseret Biologicals, Inc.
Category: homeopathic | Type: HUMAN OTC DRUG LABEL
Date: 20230411

ACTIVE INGREDIENTS: CHONDRUS CRISPUS 3 [hp_X]/1 mL; FUCUS VESICULOSUS 3 [hp_X]/1 mL; SUS SCROFA THYROID 8 [hp_X]/1 mL; CADMIUM IODIDE 12 [hp_X]/1 mL; CADMIUM SULFIDE 12 [hp_X]/1 mL; IODINE 12 [hp_X]/1 mL; RADIUM BROMIDE 12 [hp_X]/1 mL; STRONTIUM CARBONATE 12 [hp_X]/1 mL; URANYL NITRATE HEXAHYDRATE 12 [hp_X]/1 mL; ALCOHOL, X-RAY EXPOSED (1000 RAD) 30 [hp_X]/1 mL; ARNICA MONTANA 30 [hp_C]/1 mL
INACTIVE INGREDIENTS: WATER; ALCOHOL

Drug Facts:

ACTIVE INGREDIENTS:

Chondrus Crispus 3X, Fucus Vesiculosus 3X, Thyroidinum (Suis) 8X, Cadmium Iodatum 12X, Cadmium Sulphuratum 12X, Iodium 12X, Radium Bromatum 12X, Strontium Carbonicum 12X, Uranium Nitricum 12X, X-Ray 30X, 60X, 200X, 30C, 60C, Arnica Montana 30C, 60C.

HOMEOPATHIC INDICATIONS:

For temporary relief from symptoms associated with radiation exposure, including weakness, fatigue, dehydration, and occasional diarrhea.**

**These statements are based upon traditional homeopathic principles. They have not been reviewed by the Food and Drug Administration.

WARNINGS:

Keep out of reach of children. In case of overdose, contact physician or a Poison Control Center right away.

If pregnant or breast-feeding, ask a health professional before use.

Tamper seal: "Sealed for Your Protection." Do not use if seal is broken or missing.

Keep out of reach of children. In case of overdose, contact physician or a Poison Control Center right away.

DIRECTIONS:

1-10 drops under the tongue, 3 times a day or as directed by a health professional. Consult a physician for use in children under 12 years of age.

HOMEOPATHIC INDICATIONS:

For temporary relief from symptoms associated with radiation exposure, including weakness, fatigue, dehydration, and occasional diarrhea.**

**These statements are based upon traditional homeopathic principles. They have not been reviewed by the Food and Drug Administration.

INACTIVE INGREDIENTS:

Demineralized Water, 25% Ethanol

QUESTIONS:

Dist. By: Deseret Biologicals, Inc.
469 W. Parkland Drive
Sandy, UT 84070 www.desbio.com

PACKAGE LABEL DISPLAY:

DESBIO
NDC 43742-0945-1
HOMEOPATHIC
RADIATION
PLUS
1 FL OZ (30 ml)